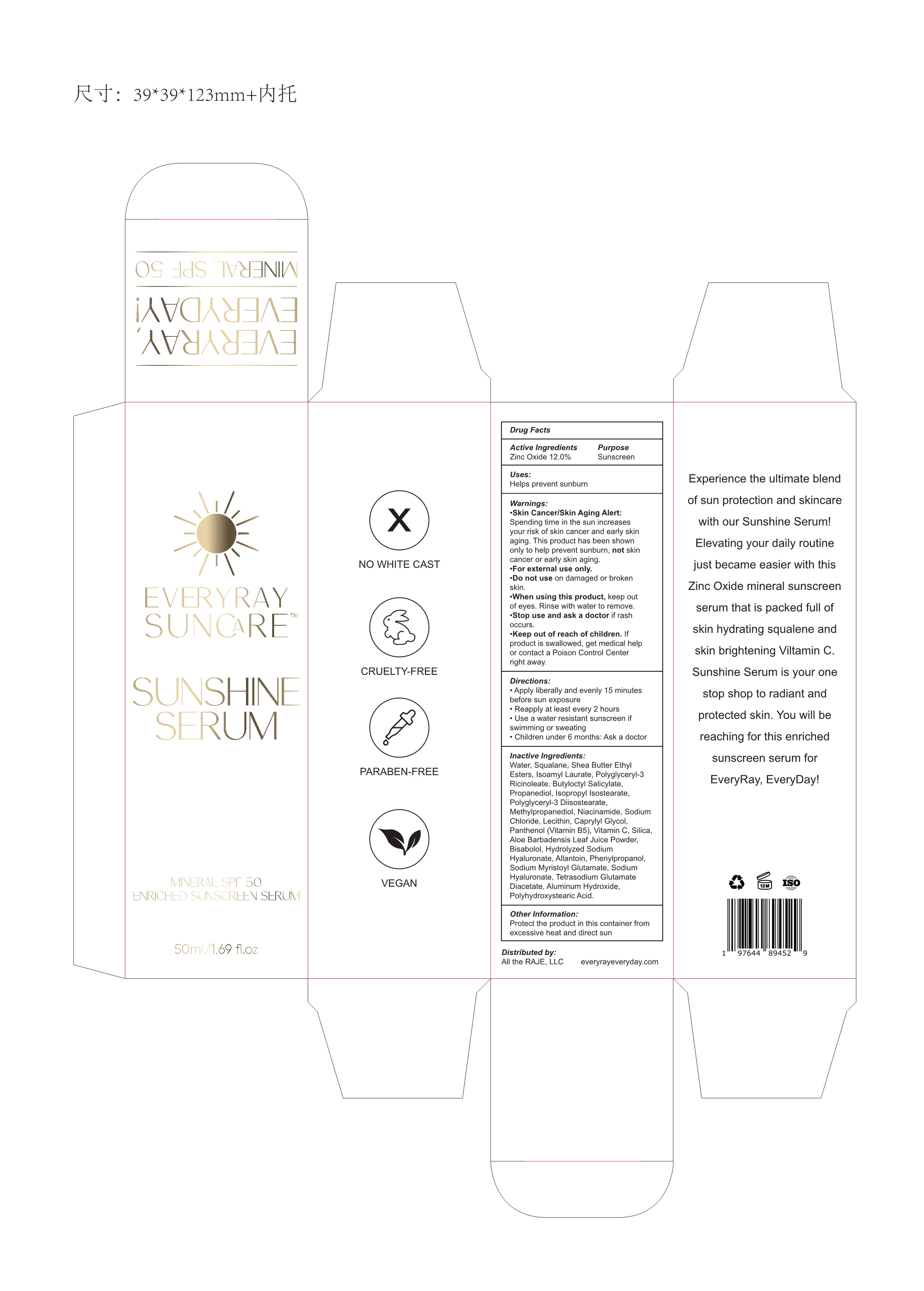 DRUG LABEL: EVERYRAY SUNCARE SUNSHINE SERUM
NDC: 83447-002 | Form: LIQUID
Manufacturer: Guangzhou Fantesy Biotechnology Co.,Ltd
Category: otc | Type: HUMAN OTC DRUG LABEL
Date: 20260105

ACTIVE INGREDIENTS: ZINC OXIDE 12 g/100 mL
INACTIVE INGREDIENTS: SODIUM CHLORIDE; SILICON DIOXIDE; WATER; SQUALANE; SHEA BUTTER ETHYL ESTERS; SODIUM MYRISTOYL GLUTAMATE; ISOAMYL LAURATE; LECITHIN, SOYBEAN; ALOE VERA LEAF; PHENYLPROPANOL; HYALURONIC ACID; POLYHYDROXYSTEARIC ACID STEARATE; POLYGLYCERYL-3 RICINOLEATE; PROPANEDIOL; NIACINAMIDE; ALUMINUM HYDROXIDE; POLYGLYCERYL-3 DIISOSTEARATE; CAPRYLYL GLYCOL; LEVOMENOL; ASCORBIC ACID; PANTHENOL; TETRASODIUM GLUTAMATE DIACETATE; ALLANTOIN; BUTYLOCTYL SALICYLATE; PYRIDOXINE HYDROCHLORIDE; METHYLPROPANEDIOL

83447-002

Active ingredients

Zinc Oxide 25%

Purpose

Sunscreen

Uses

Helps prevent sunburn

Warnings

Skin Cancer / skin Aging Alert: Spending time in the sun increasesyour risk of skin cancer and early skiraging . This product has been shownonly to help prevent sunburn , not skincancer or early skin aging.

For external use only .

Do not use on damaged or broken skin.

When using this product, keep out of eyes. Rinse with water to remove.

Stop use

Stop use and ask a doctor if rash occurs.

Keep out of reach of children . If product is swallowed . get medical help or contact a Poison Control Center right away.

Directions

Apply liberally and evenly 15 minutesbefore sun exposure.

Reapply at least every 2 hours.

Use a water resistant sunscreen if swimming or sweating.

Children under 6 months : Ask a doctor.

Other information

Protect the product in this container from excessive heat and direct sun.

Inactive ingredients

Water , Squalane , Shea Butter EthyEsters , Isoamyl Laurate , Polygly ceryl-3Ricindleate , Buty octyl SalicylatePropanediol , Isopropyl Isostearate ,Polyglyceryl-3 Diisostearate, Methyipropanediol , Niacinamide , SodiumChloride , Lecithin Caprylyl GlycolPanthenol (itamin B5) , Vitamin C , SilicaAloe Barbadensis Leaf Juice PowderBisabolol, Hvdrolvzed SodiumHyaluronate , Allantoin , PhenylpropanolSodium Myristoyl Glutamate , SodiumHyaluronate , Tetrasodium GlutamateDiacetate , Aluminum HydroxidePolyhydroxysteanic Acid